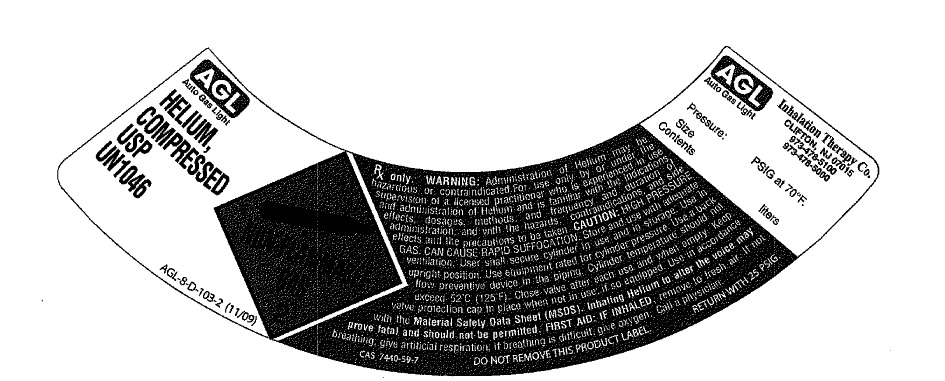 DRUG LABEL: Helium
NDC: 17575-005 | Form: GAS
Manufacturer: AGL Inhalation Therapy Co.
Category: prescription | Type: HUMAN PRESCRIPTION DRUG LABEL
Date: 20260101

ACTIVE INGREDIENTS: HELIUM 990 mL/1 L

helium

PACKAGE LABEL

AGL
Auto Gas Light
HELIUM,
COMPRESSED
USP
U.N. 1046
AGL-8-D-103-2 (11/09)
NON-FLAMMABLE GAS 2
Rx only. WARNING: Administration of helium may be hazardous or contraindicated. For use only by or under the supervision of a licensed practitioner who is experienced in the use of administration of helium and is familiar with indications, dosages and methods and frequency and duration of administration and with the hazards, contraindications and side effects and the precautions to be taken. CAUTION: HIGH PRESSURE GAS. CAN CAUSE RAPID SUFFOCATION.
Store and use with adequate ventilation. User shall secure cylinder in use and in storage. Use in upright position. Use equipment rated for cylinder pressure. Use a back flow preventive device in the piping. Cylinder temperature should not exceed 52 degrees C (125 degrees F). Close valve after each use and when empty. Keep valve protective cap in place when not in use, if so equipped. Use in accordance with the Material Safety Data Sheet (MSDS). Inhaling Helium to alter voice may prove fatal and should not be permitted. FIRST AID: IF INHALED, remove to fresh air. If not breathing, give artificial respiration. If breathing is difficult, give oxygen. Call a physician.
CAS 7440-59-7
DO NOT REMOVE THIS PRODUCT LABEL
RETURN WITH 25 PSIG.
AGL Inhalation Therapy Co. Clifton, NJ 07015
973-478-5100
973-478-5000
Pressure: PSIG at 70 degrees F.
Size
Contents liters